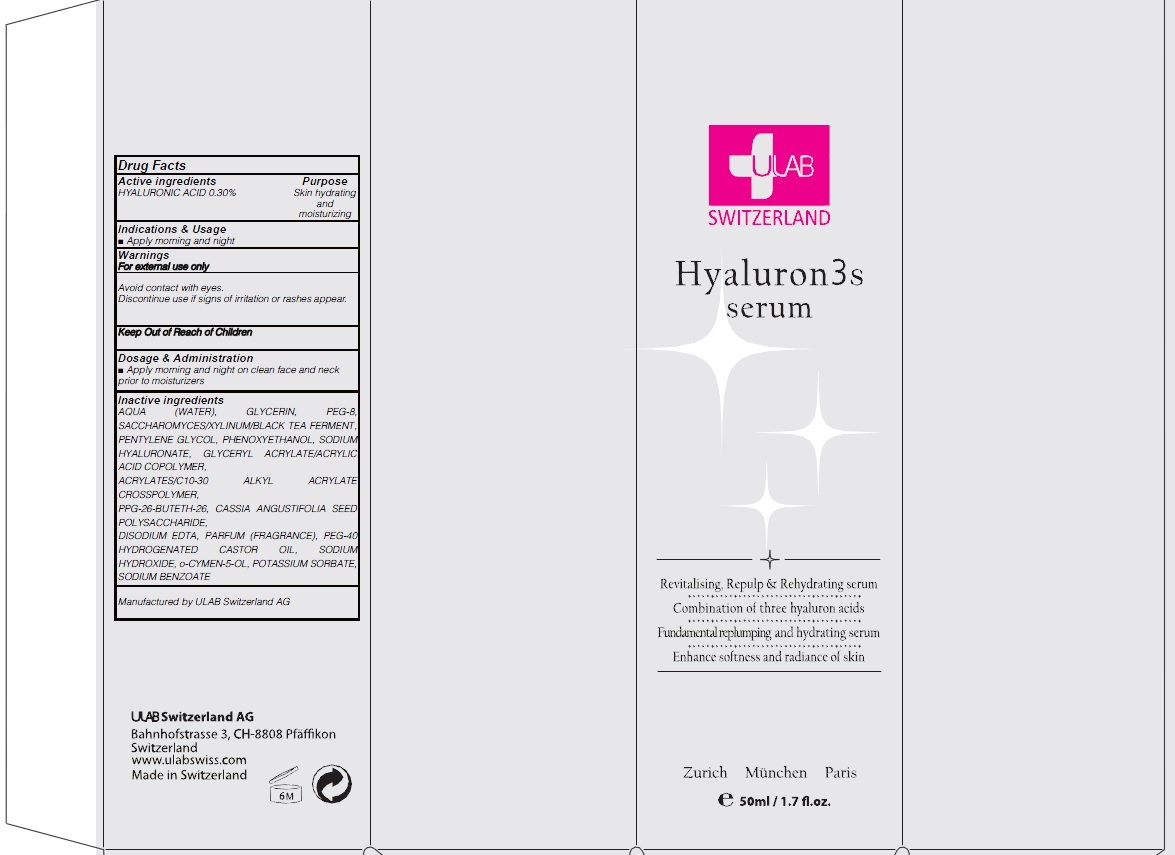 DRUG LABEL: HYALURON 3S SERUM
NDC: 71276-140 | Form: CREAM
Manufacturer: ULAB
Category: otc | Type: HUMAN OTC DRUG LABEL
Date: 20170322

ACTIVE INGREDIENTS: HYALURONIC ACID 0.15 g/50 mL
INACTIVE INGREDIENTS: WATER; GLYCERIN

ACTIVE INGREDIENT

Active ingredients: HYALURONIC ACID 0.30%

INACTIVE INGREDIENT

Inactive ingredients: AQUA (WATER), GLYCERIN, PEG-8, SACCHAROMYCES/XYLINUM/BLACK TEA FERMENT, PENTYLENE GLYCOL, PHENOXYETHANOL, SODIUM HYALURONATE, GLYCERYL ACRYLATE/ACRYLIC ACID COPOLYMER, ACRYLATES/C10-30 ALKYL ACRYLATE CROSSPOLYMER, PPG-26-BUTETH-26, CASSIA ANGUSTIFOLIA SEED POLYSACCHARIDE, DISODIUM EDTA, PARFUM (FRAGRANCE), PEG-40 HYDROGENATED CASTOR OIL, SODIUM HYDROXIDE, o-CYMEN-5-OL, POTASSIUM SORBATE, SODIUM BENZOATE

PURPOSE

Purpose: Skin hydrating and moisturizing

WARNINGS

Warnings: For external use only Avoid contact with eyes. Discontinue use if signs of irritation or rashes appear.

KEEP OUT OF REACH OF CHILDREN

INDICATIONS & USAGE

Indications & Usage: Apply morning and night

DOSAGE & ADMINISTRATION

Dosage & Administration: Apply morning and night on clean face and neck prior to moisturizers